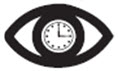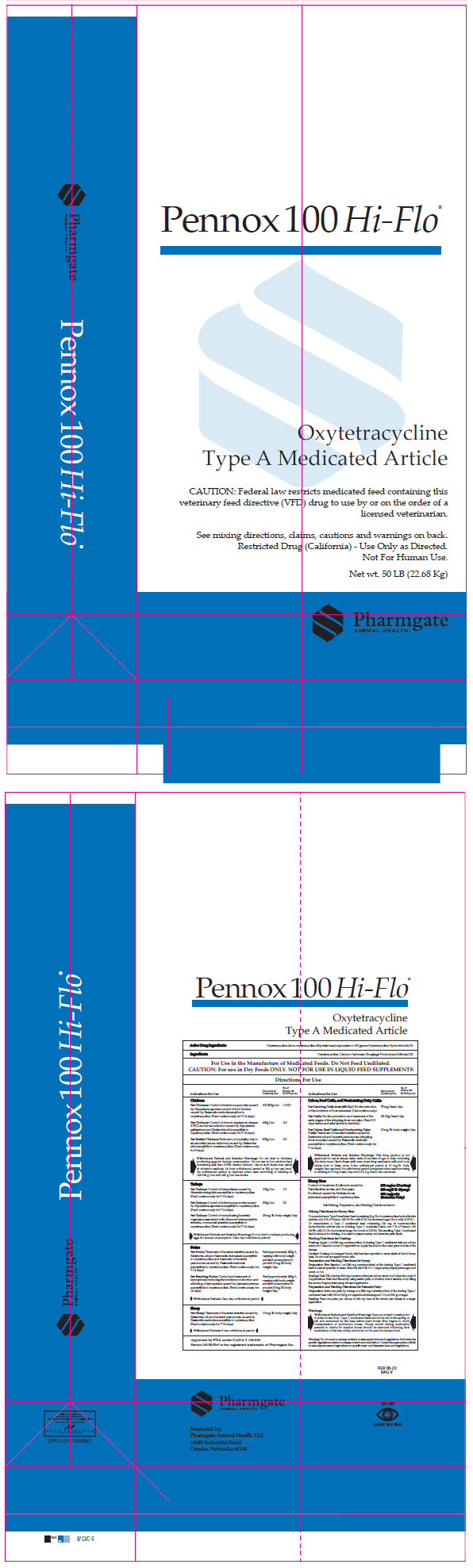 DRUG LABEL: Pennox 100 Hi-Flo
NDC: 51429-103 | Form: POWDER
Manufacturer: Pharmgate Animal Health
Category: animal | Type: VFD TYPE A MEDICATED ARTICLE ANIMAL DRUG LABEL
Date: 20231024

ACTIVE INGREDIENTS: Oxytetracycline 220 g/1 kg
INACTIVE INGREDIENTS: Calcium Carbonate; Mineral Oil

Pennox 100 Hi-Flo®

Oxytetracyline
Type A Medicated Article

DESCRIPTION

Active Drug Ingredients: Oxytetracycline (from oxytetracycline dihydrate base) equivalent to 100 grams Oxytetracycline Hydrochloride/lb.

Ingredients: Oxytetracycline, Calcium Carbonate, Roughage Products and Mineral Oil.

FOOD SAFETY WARNING

For Use in the Manufacture of Medicated Feeds. Do Not Feed Undiluted.

CAUTION: For use in Dry Feeds ONLY. NOT FOR USE IN LIQUID FEED SUPPLEMENTS

Directions For Use

INDICATIONS FOR USE

Use Level of Oxytetracycline

lbs. of Pennox 100 Hi-Flo® per ton

Chickens

For Chickens: Control of infectious synovitis caused by Mycoplasma synoviae, control of fowl cholera caused by Pasteurella multocida sensitive to oxytetracycline. (Feed continuously for 7 - 14 days)

100-200 g/ton

1.0 – 2.0

For Chickens: Control of chronic respiratory disease (CRD) and air sac infection caused by Mycoplasma gallisepticum and Escherichia coli susceptible to oxytetracycline. (Feed continuously for 7 - 14 days).

400 g/ton

4.0

For Broiler Chickens: Reduction of mortality due to air sacculitis (air sac infection) caused by Escherichia coli susceptible to oxytetracycline (Feed continuously for 5 days).

500 g/ton

5.0

Withdrawal Periods and Residue Warnings: Do not feed to chickens producing eggs for human consumption. Do not use in low calcium feed containing less than 0.55% dietary calcium. Use in such feeds may result in violative residues. 24 hour withdrawal period at 500 g/ton use levels. No withdrawal period is required when used according to labeling at 100 – 200 g/ton and 400 g/ton use levels.

Turkeys

For Turkeys: Control of hexamitiasis caused by Hexamita meleagridis susceptible to oxytetracycline. (Feed continuously for 7 - 14 days).

100 g/ton

1.0

For Turkeys: Control of infectious synovitis caused by Mycoplasma synoviae susceptible to oxytetracycline (Feed continuously for 7 - 14 days)

200g/ton

2.0

For Turkeys: Control of complicating bacterial organisms associated with bluecomb (transmissible enteritis, coronaviral enteritis) susceptible to oxytetracycline. (Feed continuously for 7 - 14 days)

25 mg/lb. body weight/day

Withdrawal Periods and Residue Warnings: Do not feed to turkeys producing eggs for human consumption. Zero-day withdrawal period.

Swine

For Swine: Treatment of bacterial enteritis caused by Escherichia coli and Salmonella choleraesuis susceptible to oxytetracycline and treatment of bacterial pneumonia caused by Pasteurella multocida susceptible to oxytetracycline. (Feed continuously for 7-14 days.)

Feed approximately 400 g/t, varying with body weight and feed consumption to provide 10 mg/lb. body weight/ day

For Breeding Swine: Control and treatment of leptospirosis (reducing the incidence of abortion and shedding of leptospirae) caused by Leptospira pomona susceptible to oxytetracycline. (Feed continuously for 14 days)

Feed approximately 400 g/t, varying with body weight and feed consumption to provide 10 mg/lb. body weight/ day

Withdrawal Periods: Zero-day withdrawal period.

Calves, Beef Cattle, and Nonlactating Dairy Cattle

For Growing cattle (over 400 lbs.): For the reduction of the incidence of liver abscesses. (Use continuously)

75 mg/head/day

For Cattle: For the prevention and treatment of the early stages of the shipping fever complex. (Feed 3-5 days before and after arrival in feedlots.)

0.5-2.0g/head/day

For Calves, Beef Cattle, and Nonlactating Dairy Cattle: Treatment of bacterial enteritis caused by Escherichia coli and bacterial pneumonia (shipping fever complex) caused by Pasteurella multocida susceptible to oxytetracycline. (Feed continuously for 7-14 days)

10 mg/lb. body weight/day

Withdrawal Periods and Residue Warnings: This drug product is not approved for use in female cattle 20 months of age or older, including dry dairy cows. Use in these cattle may cause drug residue in milk and/or in calves born to these cows. 5-day withdrawal period at 10 mg/lb. body weight/day use level. No withdrawal period is required when used according to labeling at 75 mg/head/day and 0.5-2.0g/head/day use levels.

Sheep

For Sheep: Treatment of bacterial enteritis caused by Escherichia coli and bacterial pneumonia caused by Pasteurella multocida susceptible to oxytetracycline. (Feed continuously for 7-14 days)

10 mg/lb. body weight/day

Withdrawal Periods: 5-day withdrawal period.

Honey Bees

Control of American Foulbrood caused by Paenibacillus larvae and European Foulbrood caused by Melissococcus plutonius susceptible to oxytetracycline.

200 mg/oz (Dusting)
200 mg/5 lb (Syrup)
800 mg/patty (Extender Patty)

See Mixing, Preparation and Feeding Directions below.

Mixing Directions for Honey Bees
To manufacture a Type B medicated feed containing 20g/lb of oxytetracycline hydrochloride activity, mix 5 lb of Pennox 100 Hi-Flo with 20 lb of powdered sugar (for a total of 25 lb.) To manufacture a Type C medicated feed containing 200 mg of oxytetracycline hydrochloride activity per oz (dusting Type C medicated feed), mix 7 lb of Pennox 100 Hi-Flo with 211 lb of powdered sugar (for a total of 218 lb). The resulting Type C medicated feed is fed as-is for dusting, or is used to prepare syrup and extender patty feeds.
Feeding Directions for Dusting:
Dusting: Apply 1 oz (200 mg oxytetracycline) of dusting Type C medicated feed per colony every 4 to 5 days for a total of 3 applications. Apply the dust on the outer parts or ends of the frames.
Caution: Dusting of uncapped brood cells has been reported to cause death of larval honey bees. Do not dust uncapped brood cells.
Preparation and Feeding Directions for Syrup:
Preparation: First dissolve 1 oz (200 mg oxytetracycline) of the dusting Type C medicated feed in a small quantity of water, then mix into 5 lb of 1:1 sugar syrup (equal parts sugar and water, w/w).
Feeding: Feed 5 lb of syrup (200 mg oxytetracycline) per colony every 4 to 5 days for a total of 3 applications. Bulk feed the syrup using feeder pails, or division board feeders, or by filling the combs. Prepare fresh syrup for each application.
Preparation and Feeding Directions for Extender Patty:
Preparation: Make one patty by mixing 4 oz (800 mg oxytetracycline) of the dusting Type C medicated feed with 5.8 oz (165 g) of vegetable shortening and 11.6 oz (330 g) of sugar.
Feeding: Place one patty per colony on the top bars of the brood nest frames in a single application.
Warnings:
Withdrawal Periods and Residue Warnings: Remove at least 6 weeks prior to main honey flow. Type C medicated feeds should be fed in the spring or fall and consumed by the bees before main honey flow begins to avoid contamination of production honey. Honey stored during medication periods in combs for surplus honey should be removed following final mediation of the bee colony and must not be used for human food.
Waring: Do not use in a manner contrary to state apiary laws and regulations. Each state has specific regulations relative to disease control and medication. Contact the appropriate official or state departments of agriculture for specific inter- and intrastate laws and regulations.

Approved by FDA under NADA # 138-938
Pennox 100 Hi-Flo® is the registered trademark of Pharmgate Inc.

Marketed by:
Pharmgate Animal Health, LLC
14040 Industrial Road
Omaha, NE 68144

Take TimeObserve Directions

PRINCIPAL DISPLAY PANEL - 22.68 Kg Bag

Pennox 100 Hi-Flo®

Oxytetracycline
Type A Medicated Article

CAUTION: Federal law restricts medicated feed containing this
veterinary feed directive (VFD) drug to use by or on the order of a
licensed veterinarian.

See mixing directions, claims, cautions and warnings on back.
Restricted Drug (California) - Use Only as Directed.
Not For Human Use.

Net wt. 50 LB (22.68 Kg)

Pharmgate
ANIMAL HEALTH